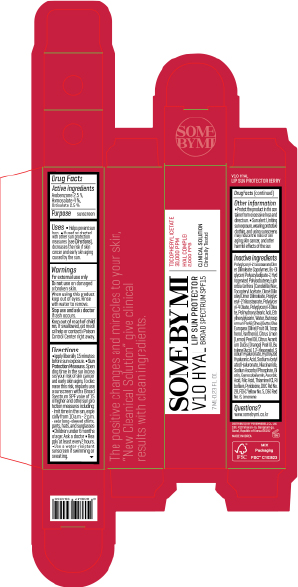 DRUG LABEL: SOME BY MI V10 HYAL LIP SUN PROTECTOR BERRY
NDC: 74472-702 | Form: LIPSTICK
Manufacturer: PERENNEBELL Co., Ltd
Category: otc | Type: HUMAN OTC DRUG LABEL
Date: 20250209

ACTIVE INGREDIENTS: HOMOSALATE 0.28 g/7 mL; OCTISALATE 0.175 g/7 mL; AVOBENZONE 0.175 g/7 mL
INACTIVE INGREDIENTS: BUTYLENE GLYCOL; ASCORBIC ACID; ETHYLHEXYLGLYCERIN; CITRUS LIMON (LEMON) PEEL OIL; WATER; FD&C YELLOW NO. 5; NIACINAMIDE; BIOTIN; THIAMINE HCL; RIBOFLAVIN; POLYGLYCERYL-6 OLEATE; DIMER DILINOLEYL DIMER DILINOLEATE; POLYGLYCERYL-4 OLEATE; SODIUM ACETYLATED HYALURONATE; D&C RED NO. 6; CITRUS AURANTIUM DULCIS (ORANGE) PEEL OIL; BUTYROSPERMUM PARKII (SHEA) BUTTER; SODIUM HYALURONATE; TOCOPHEROL; CYANOCOBALAMIN; FOLIC ACID; PYRIDOXINE; POLYGLYCERYL-2 TRIISOSTEARATE; SODIUM ASCORBYL PHOSPHATE; ALPHA-TOCOPHEROL ACETATE; OLEA EUROPAEA (OLIVE) FRUIT OIL; PANTHENOL; BIS-DIGLYCERYL POLYACYLADIPATE-2; EUPHORBIA CERIFERA (CANDELILLA) WAX; 1,2-HEXANEDIOL; D&C RED NO. 28; LIMONENE, (+)-

SOME BY MI V10 HYAL LIP SUN PROTECTOR BERRY

Active ingredients

Avobenzone 2.5 %
Homosalate 4 %
Octisalate 2.5

Purpose

sunscreen

Uses

■ Helps prevent sun burn. ■ If used as directed with other sun protection measures (see Directions), decreases the risk of skin cancer and early skin aging caused by the sun.

Warnings

For external use only

Do not use

on damaged or broken skin.

When using this product

keep out of eyes. Rinse with water to remove.

Stop use and ask a doctor

if rash occurs.

Keep out of reach of children.

If swallowed, get medi cal help or contact a Poison Control Center right away

Directions

■ Apply liberally 15 minutes before sun exposure.

■ Sun Protection Measures. Spen ding time in the sun increa ses your risk of skin cancer and early skin aging. To dec rease this risk, regularly use a sunscreen with a Broad Spectrum SPF value of 15 or higher and other sun pro tection measures including:
• limit time in the sun, espe cially from 10 a.m. – 2 p.m.
• wear long-sleeved shirts, pants, hats, and sunglasses

■ Children under 6 months of age: Ask a doctor

■ Reapply at least every 2 hours.

■ Use a water-resistant sunscreen if swimming or sweating.

Other information

■ Protect the product in this con tainer from excessive heat and direct sun. ■ Sun alert: Limiting sun exposure, wearing protective clothing, and using sunscreens may reduce the risks of skin aging, skin cancer, and other harmful effects of the sun.

Inactive ingredients

Polyglyceryl-2 Isostearate/Dimer Dilinoleate Copolymer, Bis-Diglyceryl Polyacyladipate-2, Hy drogenated Polyisobutene, Water, Euphorbia Cerifera(Candeli lla) Wax, Tocopheryl Acetate, Dimer Dilinoleyl Dimer Dilinoleate, Polyglyceryl-2 Triisostearate, Polyglyceryl-4 Oleate, Polyglyceryl-6 Oleate, Polyhydroxystearic Acid, Ethylhexylglycerin, Butyrospermum Parkii (Shea) Butter, Olea Europaea (Olive) Fruit Oil, Tocopherol, Panthenol, Citrus Limon (Lemon) Peel Oil, Citrus Aurantium Dulcis (Orange) Peel Oil, Butylene Glycol, 1,2-Hexanediol, Sodium Hyaluronate, Hydrolyzed Hyaluronic Acid, Sodium Acetylated Hyaluronate, Niacinamide, Sodium Ascorbyl P hosphate, Biotin, Cyanocobalamin, Ascorbic Acid, Folic Acid, Thiamine HCl, Riboﬂavin, Pyridoxine, D&C Red No. 28, FD&C Yellow No. 5, D&C Red No. 6, Limonene

Questions?

www.somebymi.co.kr